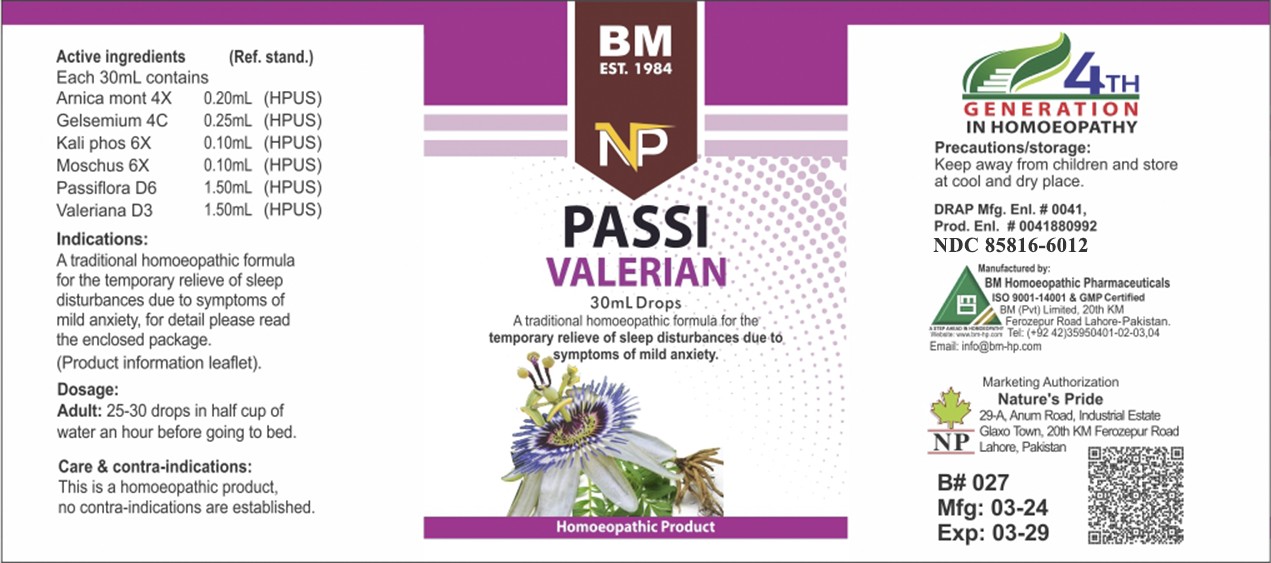 DRUG LABEL: PASSI VALERIAN
NDC: 85816-6012 | Form: LIQUID
Manufacturer: BM Private Limited
Category: homeopathic | Type: HUMAN OTC DRUG LABEL
Date: 20250731

ACTIVE INGREDIENTS: ARNICA MONTANA 4 [hp_X]/1 mL; GELSEMIUM SEMPERVIRENS ROOT 4 [hp_C]/1 mL; VALERIAN 3 [hp_X]/1 mL; DIBASIC POTASSIUM PHOSPHATE 6 [hp_X]/1 mL; MOSCHUS MOSCHIFERUS MUSK SAC RESIN 6 [hp_X]/1 mL; PASSIFLORA INCARNATA FLOWERING TOP 6 [hp_X]/1 mL
INACTIVE INGREDIENTS: ALCOHOL 0.96 mL/1 mL

BM HOMEOPATHIC LIQUID PASSI VALERIAN

DOSAGE AND ADMINISTRATION

25-30 drops in half cup of water an hour before going to bed

ACTIVE INGREDIENT

arnica montana, gelsemium, kali phos, moschus, passiflora, valeriana

INACTIVE INGREDIENT

ALCOHOL

INDICATIONS AND USAGE

A traditional homoeopathic formula for the temporary relieve of sleep disturbances due to symptoms of mild anxiety, for detail please read the enclosed package.
(Product information leaflet).

PURPOSE

A traditional homoeopathic formula for the temporary relieve of sleep disturbances due to symptoms of mild anxiety, for detail please read the enclosed package.
(Product information leaflet).

CONTRAINDICATIONS

Care & contra-indications:
This is a homoeopathic remedy, no contra-indications are established.

WARNINGS

Precautions/storage:
Keep away from children and store at cool and dry place.

KEEP OUT OF REACH OF CHILDREN

Precautions/storage:
Keep away from children and store at cool and dry place.